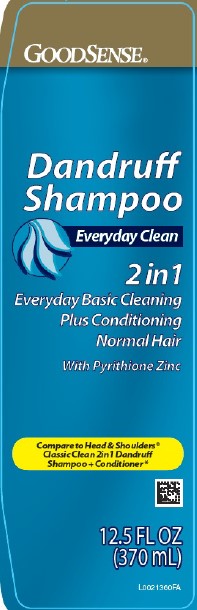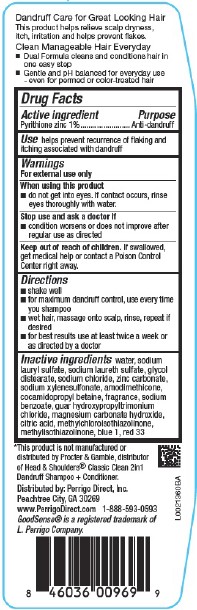 DRUG LABEL: Everyday Clean
NDC: 50804-311 | Form: SHAMPOO
Manufacturer: Perrigo Direct, Inc
Category: otc | Type: HUMAN OTC DRUG LABEL
Date: 20260219

ACTIVE INGREDIENTS: PYRITHIONE ZINC 10 mg/1 mL
INACTIVE INGREDIENTS: WATER; SODIUM LAURYL SULFATE; SODIUM LAURETH SULFATE; GLYCOL DISTEARATE; SODIUM CHLORIDE; ZINC CARBONATE; SODIUM XYLENESULFONATE; AMODIMETHICONE (800 CST); COCAMIDOPROPYL BETAINE; SODIUM BENZOATE; GUAR HYDROXYPROPYLTRIMONIUM CHLORIDE (1.7 SUBSTITUENTS PER SACCHARIDE); MAGNESIUM CARBONATE HYDROXIDE; CITRIC ACID MONOHYDRATE; METHYLCHLOROISOTHIAZOLINONE; METHYLISOTHIAZOLINONE; FD&C BLUE NO. 1; D&C RED NO. 33

Good Sense 311.007/311.007AK-AN
Dandruff Shampoo, Everyday Clean 2 in 1

Dandruff Care for Great Looking Hair

This product helps relieve scalp dryness, itch, irritation and helps prevent flakes.

Clean Manageable Hair Everyday

- Dual Formula cleans and conditions hair in on easy step
- Gentle and pH balances for everyday use - even for permed or color-treated hair

Active ingredient

Pyrithione zinc 1%

Purpose

Anti-dandruff

Use

Helps prevent recurrence of flaking and itching associated with dandruff

Warnings

For external use only

When using this product

- do not get into eyes. If contact occurs, rinse eyes thoroughly with water.

Stop use and ask a doctor if

- condition worsens or does not improve after regular use as directed

Keep out of reach of children.

If swallowed, get medical help or contact a Poison Control Center right away.

Directions

- shake well
- for maximum dandruff control, use every time you shampoo
- wet hair, massage onto scalp, rinse, repeat if desired
- for best results use at least twice a week or as directed by a doctor

Inactive ingredients

water, sodium lauryl sulfate, sodium laureth sulfate, glycol distearate, sodium chloride, zinc carbonate, sodium xylenesulfonate, amodimethicone, cocamidopropyl betaine, fragrance, sodium benzoate, guar hydroxypropyltrimonium chloride, magnesium carbonate hydroxide, citric acid, methylchloroisothiazolinone, methylisothiazolinone, blue 1, red 33

Disclaimer

*This product is not manufactured or distributed by Procter & Gamble, the distributor of Head & Shoulders® Classic Clean 2 in 1 Pyrithione Zinc Dandruff Shampoo + Conditioner.

Adverse reaction

Distributed By: Perrigo Direct, Inc.

Peachtree City, GA 30269

www.PerrigoDirect.com

1-888-593-0593

GoodSense® is a registered trademark of L. Perrigo Company.

Principal display panel

GoodSense®

Dandruff Shampoo

Everyday Clean

2 in 1

Everyday Basic Cleaning

Plus Conditioning

Normal Hair

With Pyrithione Zinc

Compare to Head & Shoulders®Classic Clean 2in1 Dandruff Shampoo + Conditioner*

12.5 FL OZ (370 mL)